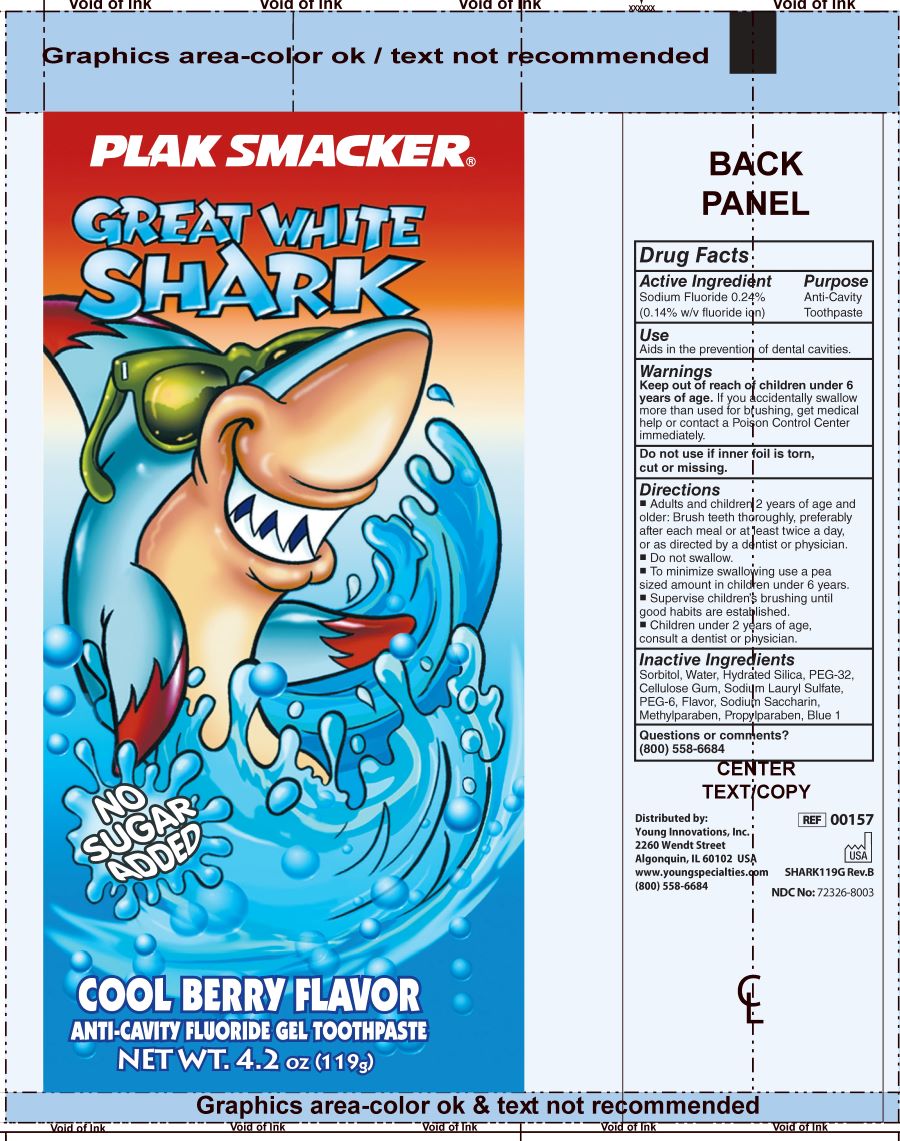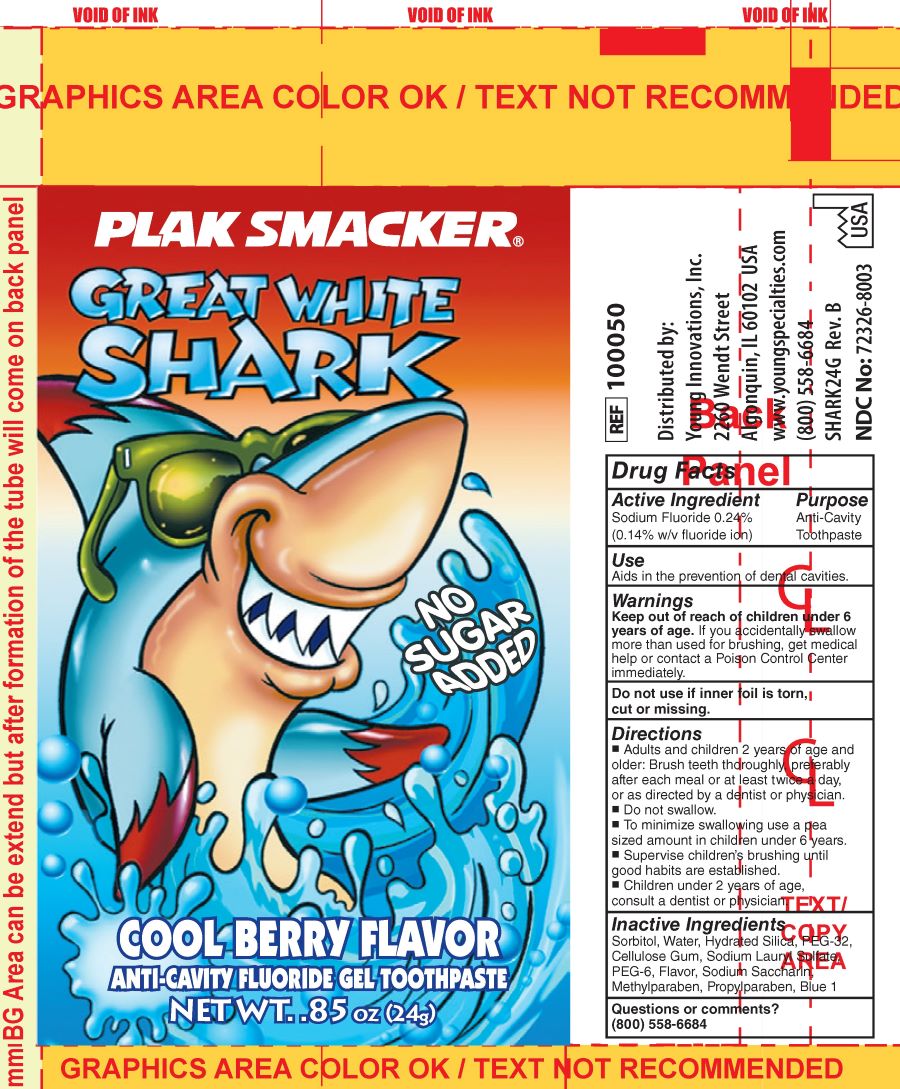 DRUG LABEL: Plak Smacker GREAT WHITE SHARK
NDC: 72326-8003 | Form: PASTE
Manufacturer: YOUNG PS ACQUISITION, LLC
Category: otc | Type: HUMAN OTC DRUG LABEL
Date: 20251104

ACTIVE INGREDIENTS: SODIUM FLUORIDE 1.4 mg/1 g
INACTIVE INGREDIENTS: CARBOXYMETHYLCELLULOSE; RASPBERRY; POLYETHYLENE GLYCOL 300; POLYETHYLENE GLYCOL 1450; SODIUM LAURYL SULFATE; METHYLPARABEN; FD&C BLUE NO. 1; PROPYLPARABEN; SORBITOL; HYDRATED SILICA; SACCHARIN SODIUM; WATER

Plak Smacker GREAT WHITE SHARK ANTI-CAVITY

Active Ingredient

Sodium Fluoride 0.24%

(0.14% w/v Fluoride ion)

Purpose

Anticavity toothpaste

Purpose

Anti-Cavity

Toothpaste

Use

Aids in the prevention of dental cavities.

Warnings

Keep out of the reach of children under 6 years of age. If more than used for brushing is accidentally swallowed, get medical help or contact a Poison Control Center right away.

Do not use if inner foil is torn, cut, or missing.

Warnings

Keep out of the reach of children under 6 years of age. If you accidentally swallow more than used for brushing, get medical help or contact a Poison Control Center immediately.

Do not use if inner foil is torn, cut or missing.

Directions

- Adults and children 2 years of age and older: Brush teeth thoroughly, preferably after each meal or at least twice a day, or as directed by a dentist or physician.
- Do not swallow.
- To minimize swallowing use a pea sized amount in children under 6 years.
- Supervise children's brushing until good habits are established.
- Children under 2 years of age, consult a dentist or physician.

Inactive Ingredients

Sorbitol, Water, Hydrated Silica, PEG-32, Cellulose Gum, Sodium Lauryl Sulfate, PEG-6, Flavor, Sodium Saccharin, Methylparaben, Propylparaben, Blue1

Questions or comments?

(800) 558-6684

PACKAGE LABEL

PLAK SMACKER®

GREAT WHITE SHARK

NO SUGAR ADDED

COOL BERRY FLAVOR

ANTI-CAVITY FLUORIDE GEL TOOTHPASTE

NET WT. 4.2oz (119g)